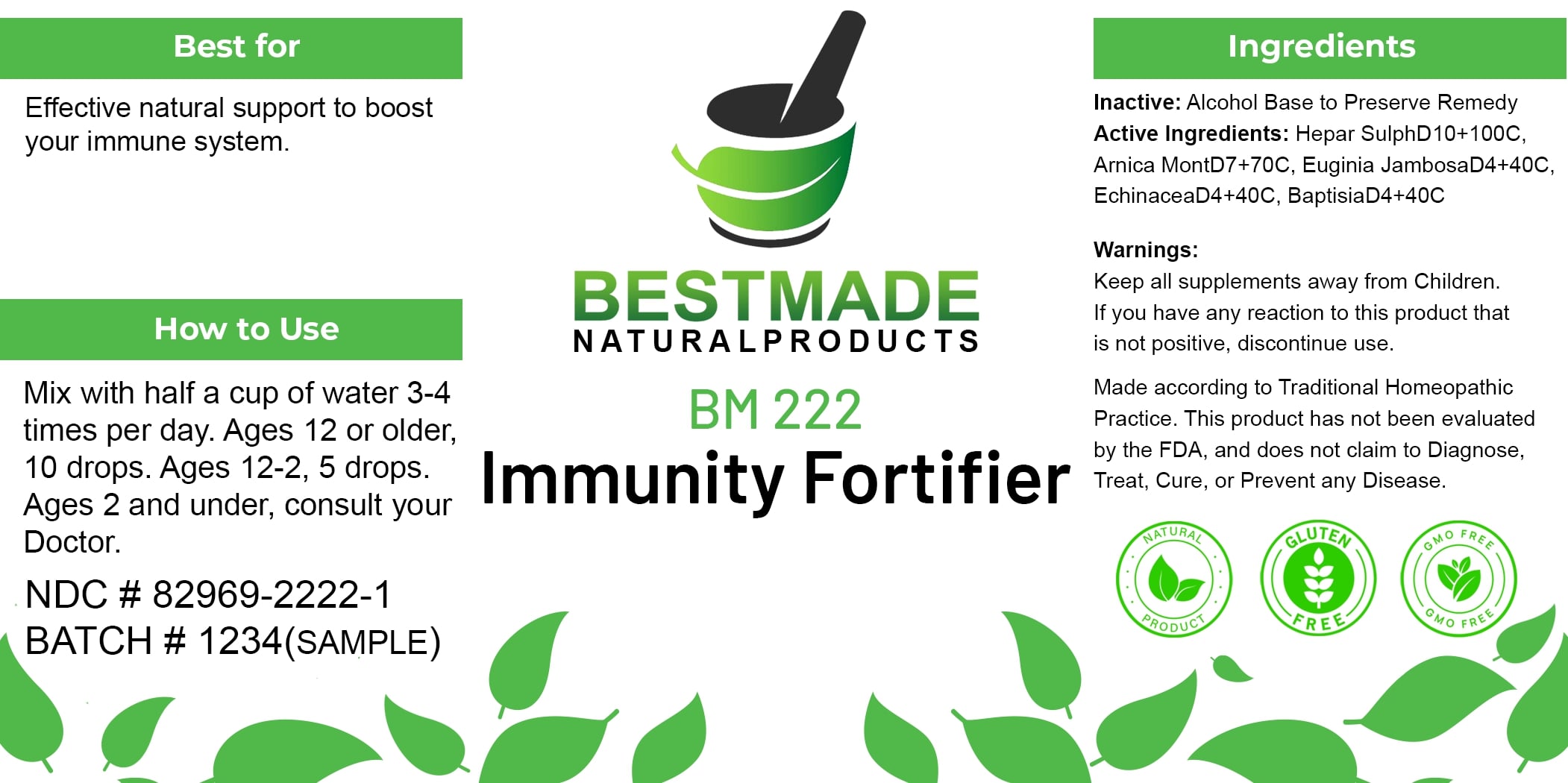 DRUG LABEL: Bestmade Natural Products BM222
NDC: 82969-2222 | Form: LIQUID
Manufacturer: Bestmade Natural Products
Category: homeopathic | Type: HUMAN OTC DRUG LABEL
Date: 20241218

ACTIVE INGREDIENTS: CALCIUM SULFIDE 30 [hp_C]/30 [hp_C]; SYZYGIUM JAMBOS WHOLE 30 [hp_C]/30 [hp_C]; ARNICA MONTANA 30 [hp_C]/30 [hp_C]; BAPTISIA TINCTORIA 30 [hp_C]/30 [hp_C]; ECHINACEA, UNSPECIFIED 30 [hp_C]/30 [hp_C]
INACTIVE INGREDIENTS: ALCOHOL 30 [hp_C]/30 [hp_C]

BM222

DOSAGE AND ADMINISTRATION

How to Use
Mix with half a cup of water 3-4 times per day. Ages 12 or older, 10 drops. Ages 12-2, 5 drops. Ages 2 and under, consult your Doctor.

INDICATIONS AND USAGE

Best for
Effective natural support to boost your immune system.

INACTIVE INGREDIENT

Ingredients
Inactive: Alcohol Base to Preserve Remedy

ACTIVE INGREDIENT

Active Ingredients: Hepar SulphD10+100C, Arnica MontD7+70C, Eugenia JambosaD4+40C, EchinaceaD4+40C, BaptisiaD4+40C

Warnings:
Keep all supplements away from Children.
If you have any reaction to this product that is not positive, discontinue use.

Made according to Traditional Homeopathic Practice. This product has not been evaluated by the FDA, and does not claim to Diagnose, Treat, Cure, or Prevent any Disease.

PURPOSE

Best for
Effective natural support to boost your immune system.

Warnings:
Keep all supplements away from Children.
If you have any reaction to this product that is not positive, discontinue use.

Made according to Traditional Homeopathic Practice. This product has not been evaluated by the FDA, and does not claim to Diagnose, Treat, Cure, or Prevent any Disease.

Entire package label